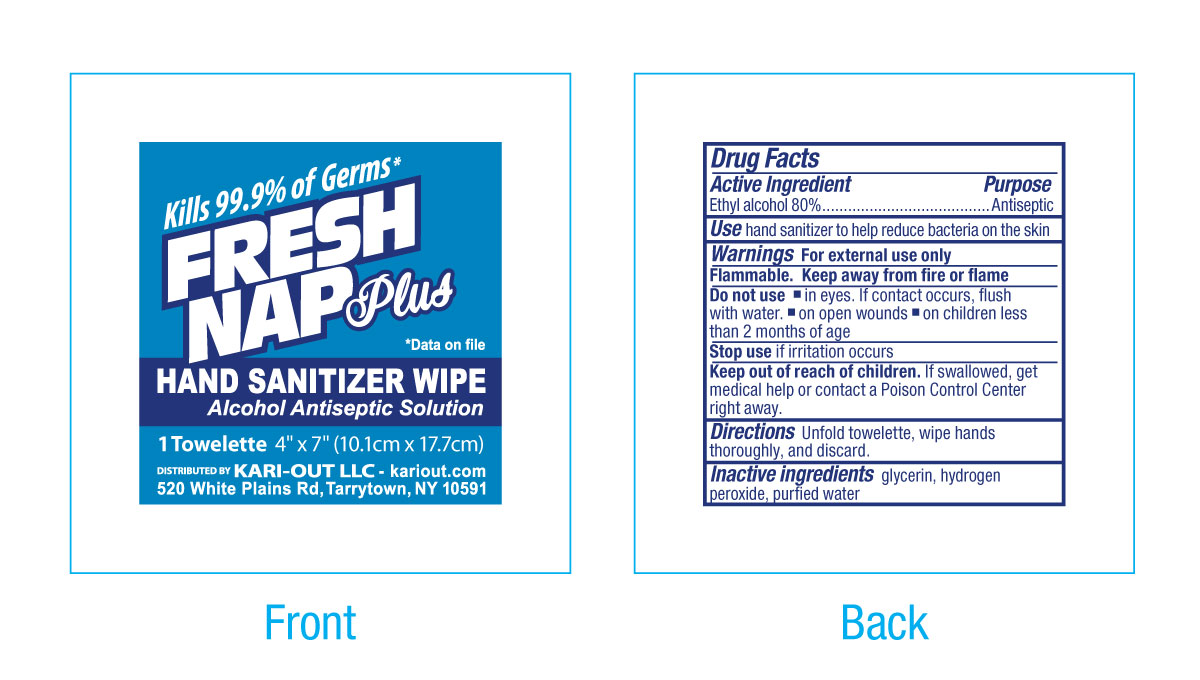 DRUG LABEL: Fresh Nap Plus Hand Sanitizer
NDC: 0924-0255 | Form: SWAB
Manufacturer: Acme United Corporation
Category: otc | Type: HUMAN OTC DRUG LABEL
Date: 20241126

ACTIVE INGREDIENTS: ALCOHOL 80 mL/100 mL
INACTIVE INGREDIENTS: HYDROGEN PEROXIDE; GLYCERIN; WATER

Fresh Nap Plus Hand Sanitizer Wipe

Active Ingredient

Ethyl Alcohol 80%

Purpose

Antiseptic

Use

hand sanitizer to help reduce bacteria on the skin

Warnings

For external use only

WARNINGS

Flammable. Keep away from fire or flame

Do not use

▪in eyes. If contact occurs, flush with water.

▪on open wounds

▪on children less than 2 months of age

Stop use

if irritation occurs

Keep out of reach of children. If swallowed, get medical help or contact a Poison Control Center right away.

Directions

Unfold towelette, wipe hands thoroughly, and discard.

Inactive Ingredients

glycerin, hydrogen peroxide, purified water

packette label